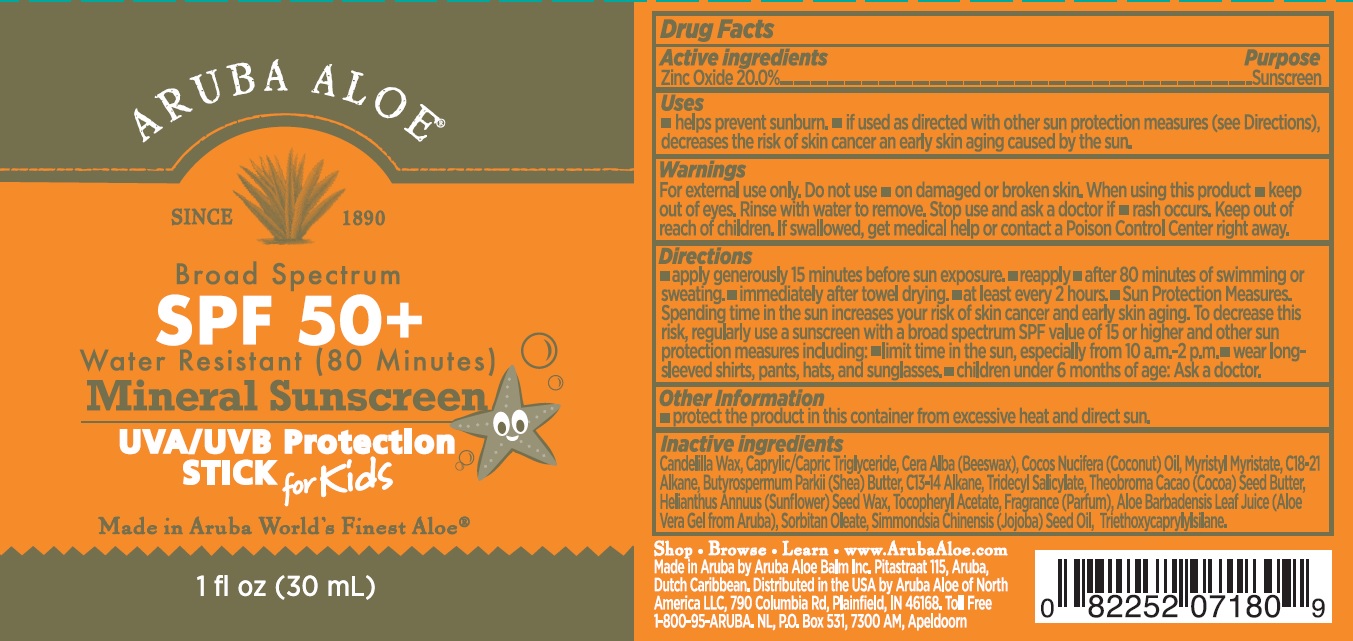 DRUG LABEL: Broad Spectrum SPF50 Water Resistant (80 minutes) Mineral Sunscreen UVA UVB Protection Stick for Kids
NDC: 53675-205 | Form: STICK
Manufacturer: Aruba Aloe Balm NV
Category: otc | Type: HUMAN OTC DRUG LABEL
Date: 20231106

ACTIVE INGREDIENTS: ZINC OXIDE 200 mg/1 mL
INACTIVE INGREDIENTS: CANDELILLA WAX; MEDIUM-CHAIN TRIGLYCERIDES; YELLOW WAX; COCONUT OIL; MYRISTYL MYRISTATE; SHEA BUTTER; TRIDECYL SALICYLATE; COCOA BUTTER; HELIANTHUS ANNUUS SEED WAX; .ALPHA.-TOCOPHEROL ACETATE; ALOE VERA LEAF; SORBITAN MONOOLEATE; JOJOBA OIL; TRIETHOXYCAPRYLYLSILANE

Broad Spectrum SPF50+ Water Resistant (80 minutes) Mineral Sunscreen UVA/UVB Protection Stick for Kids

Active ingredients

Zinc Oxide 20.0%

Purpose

Sunscreen

Uses

- helps prevent sunburn.
- if used as directed with other sun protection measures (see Directions), decreases the risk of skin cancer an early skin aging caused by the sun.

Warnings

For external use only.

Do not use

- on damaged or broken skin.

When using this product

- keep out of eyes. Rinse with water to remove.

Stop use and ask a doctor if

- rash occurs.

Keep out of reach of children.

If swallowed, get medical help or contact a Poison Control Center right away.

Directions

•apply generously 15 minutes before sun exposure. • reapply • after 80 minutes of swimming or sweating. • immediately after towel drying • at least every 2 hours. • Sun Protection Measures. Spending time in the sun increases your risk of skin cancer and early skin aging. To decrease this risk, regularly measures including: • limit time in the sun, especially from 10 a.m.-2 p.m. • wear long sleeved shirts, pants, hats, and sunglasses. • children under 6 months of age: Ask a doctor.

Other Information

- protect the product in this container from excessive heat and direct sun.

Inactive ingredients

Candelilla Wax, Caprylic/Capric Triglyceride, Cera Alba (Beeswax), Cocos Nucifera (Coconut) Oil, Myristyl Myristate, C18-20 Alkane, Butyrospermum Parkii (Shea) Butter, C13-14 Alkane, Tridecyl Salicylate, Theobroma Cacao (Cocoa) Seed Butter, Helianthus Annuus (Sunflower) Seed Wax, Tocopheryl Acetate, Fragrance (Parfum), Aloe Barbadensis Leaf Juice (Aloe Vera Gel from Aruba), Sorbitan Oleate, Simmondsia Chinensis (Jojoba) Seed Oil, Triethoxycaprylylsilane.